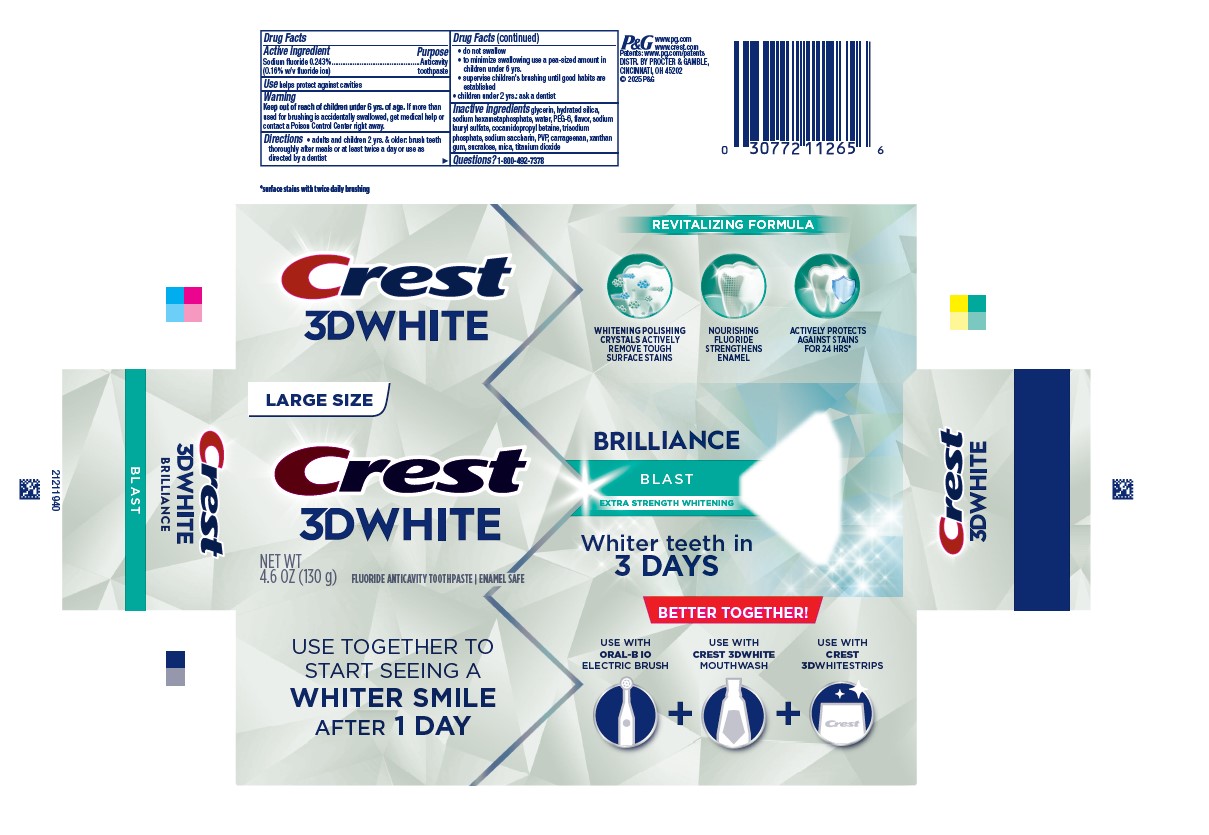 DRUG LABEL: Crest 3D White
NDC: 37000-916 | Form: PASTE, DENTIFRICE
Manufacturer: The Procter & Gamble Manufacturing Company
Category: otc | Type: HUMAN OTC DRUG LABEL
Date: 20251217

ACTIVE INGREDIENTS: SODIUM FLUORIDE 1.6 mg/1 g
INACTIVE INGREDIENTS: GLYCERIN; WATER; HYDRATED SILICA; COCAMIDOPROPYL BETAINE; SACCHARIN SODIUM; XANTHAN GUM; SUCRALOSE; POVIDONE, UNSPECIFIED; MICA; TITANIUM DIOXIDE; SODIUM PHOSPHATE, TRIBASIC, ANHYDROUS; CARRAGEENAN; SODIUM LAURYL SULFATE; SODIUM POLYMETAPHOSPHATE; POLYETHYLENE GLYCOL 300

Crest® 3D White ™
Brilliance Blast

Drug Facts

Active ingredient

Sodium fluoride 0.243% (0.16% w/v fluoride ion)

Purpose

Anticavity toothpaste

Use

helps protect against cavities

Warning

Keep out of reach of children under 6 yrs. of age. If more than used for brushing is accidentally swallowed, get medical help or contact a Poison Control Center right away.

Directions

- adults and children 2 yrs. & older: brush teeth thoroughly after meals or at least twice a day or use as directed by a dentist
  - do not swallow
  - to minimize swallowing use a pea-sized amount in children under 6
  - supervise children's brushing until good habits are established
- children under 2 yrs.: ask a dentist

Inactive ingredients

glycerin, hydrated silica, sodium hexametaphosphate, water, PEG-6, flavor, sodium lauryl sulfate, cocamidopropyl betaine, trisodium phosphate, sodium saccharin, PVP, carrageenan, xanthan gum, sucralose, mica, titanium dioxide

Questions?

1-800-492-7378

DISTR. BY PROCTER & GAMBLE, CINCINNATI, OH 45202

PRINCIPAL DISPLAY PANEL - 130g Tube Carton

LARGE SIZE

CREST

3D WHITE

BRILLIANCE

BLAST

EXTRA STRENGTH WHITENING

NET WT 4.6 OZ (130g)

FLUORIDE ANTICAVITY TOTHPASTE

ENAMEL SAFE

WHITER TEETH IN 3 DAYS